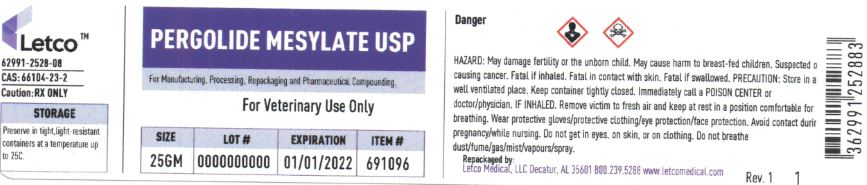 DRUG LABEL: Pergolide Mesylate
NDC: 62991-2528 | Form: POWDER
Manufacturer: LETCO MEDICAL, LLC
Category: other | Type: BULK INGREDIENT - ANIMAL DRUG
Date: 20240718

ACTIVE INGREDIENTS: PERGOLIDE MESYLATE 1 g/1 g

Pergolide Mesylate USP

PACKAGE LABEL

Pergolide Mesylate USP 25gm